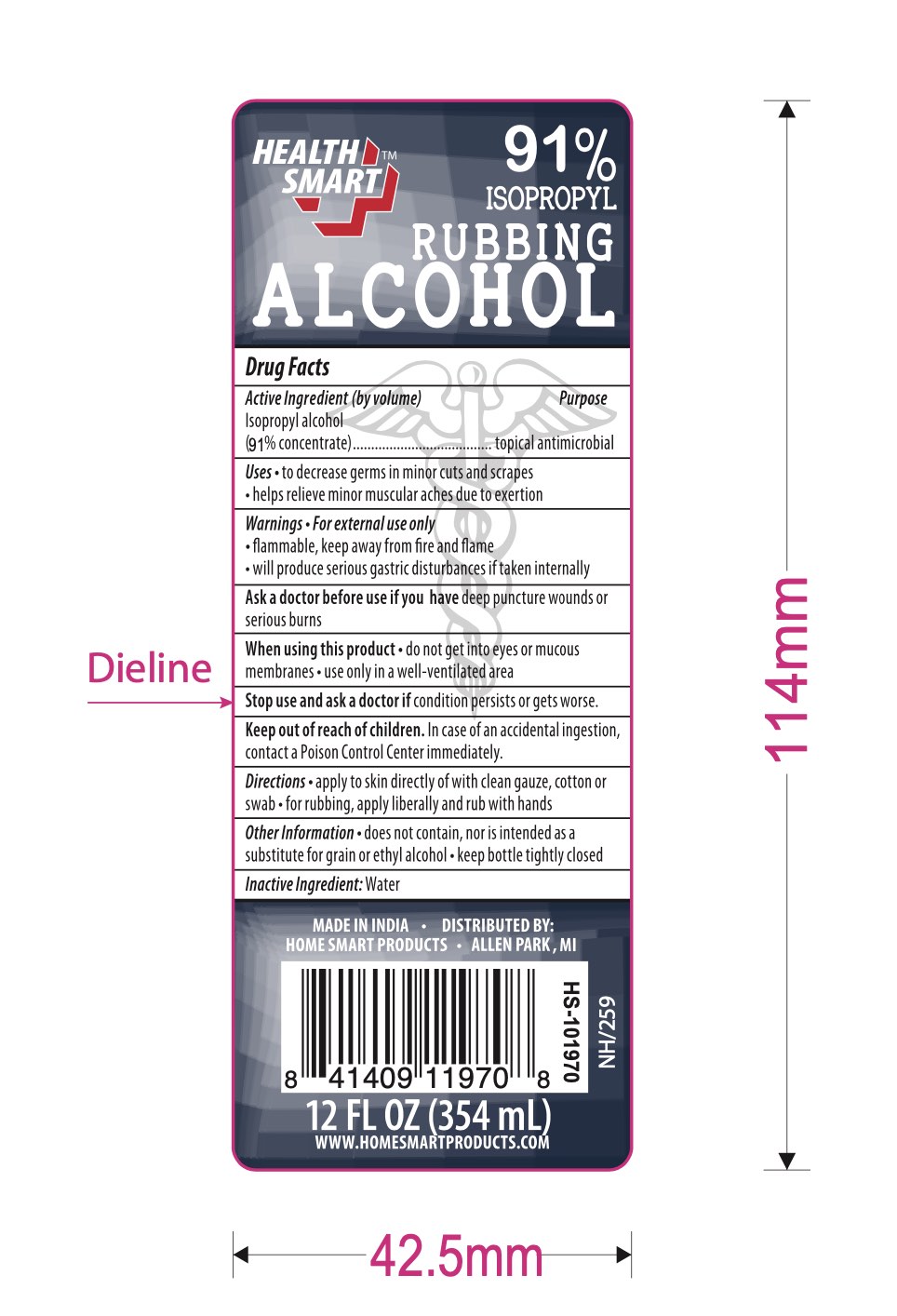 DRUG LABEL: 91% Isopropyl Rubbing Alcohol
NDC: 30400-601 | Form: LIQUID
Manufacturer: Jell Pharmaceuticals Pvt Ltd.
Category: otc | Type: HUMAN OTC DRUG LABEL
Date: 20251111

ACTIVE INGREDIENTS: ISOPROPYL ALCOHOL 91 mL/100 mL
INACTIVE INGREDIENTS: WATER

91%ISOPROPYL Rubbing Alcohol

Active ingredients (by volume):

Isopropyl alcohol

(91% conc.)

Purpose

first aid antiseptic

Uses

• First aid to help prevent the risk of infection in minor cuts, scrapes and burns

Warnings

• For external use only; flammable, keep away from fire or flame, heat, spark, electrical, etc.

Ask a doctor before use if you have

• Deep punctured wounds, animal bites or serious burns

When using this product

• Do not get into eyes

• Do not apply over large areas of the body

• Do not use longer than one week unless directed by a doctor

Stop using this product if

• Condition persists or gets worse

KEEP OUT OF REACH OF CHILDREN

Keep this drug out of the reach of children

• In case of an accidental ingestion, seek professional assistance or contact a Poison control center (1-800-222-1222) immediately

Directions

• Clean effected area

• Apply small amount of this product on the area 1-3 times daily

• May be covered with a sterile bandage

• If bandaged, let dry first

Other information

• Store at room temperature

• Does not contain, nor is intended as a substitute for grain or ethyl alcohol. Will produce serious gastric disturbances if taken internally

Inactive Ingredient

Water(Aqua)

AS 9175

Use only in a well ventilated area

Fumes may be harmful

WARNING FLAMMABLE

keep away from fire or flame!

91% by volume

TAMPER EVIDENT: DO NOT USE IF THE UNDER CAP SAFETY FOIL IS BROKEN OR MISSING

Made in India

DISTRIBUTED:

JMD ALLSTAR IMPEX INC

120 ETHEL ROAD, PISCATAWAY,

NJ 08854, USA

DESIGNED IN THE USA